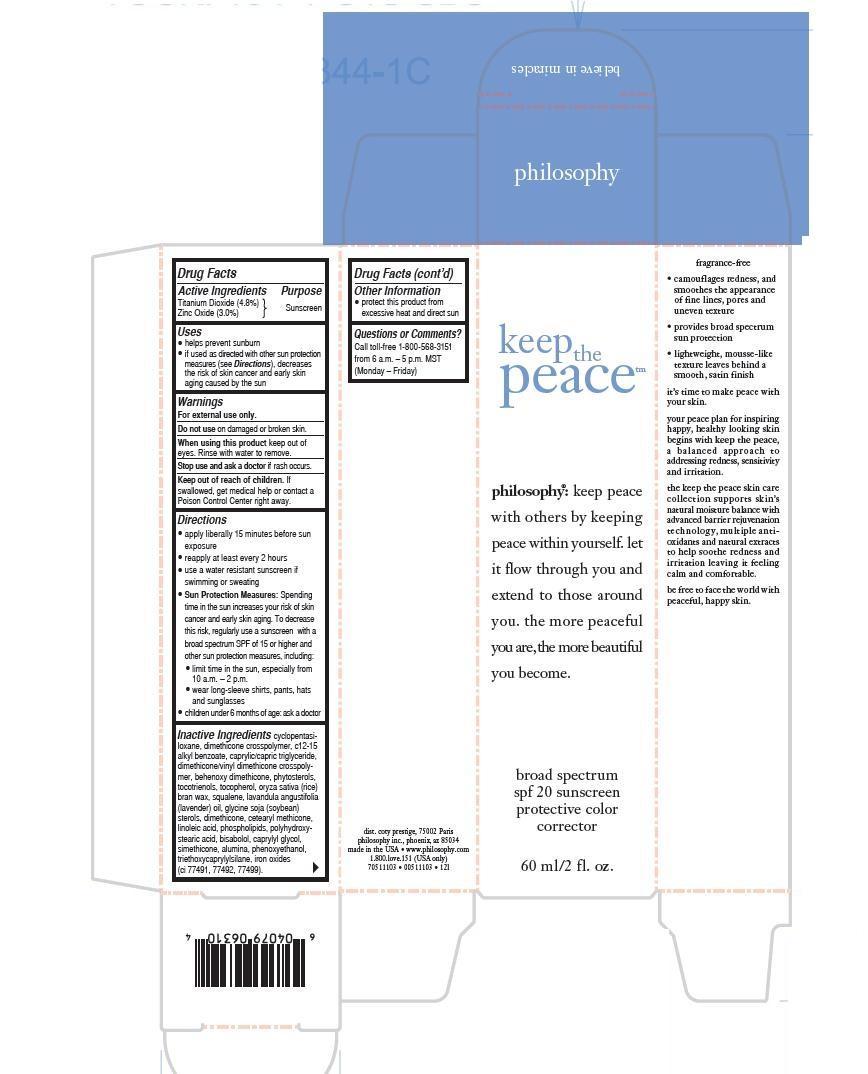 DRUG LABEL: Keep the Peace
NDC: 50184-1031 | Form: LOTION
Manufacturer: Philosophy, Inc.
Category: otc | Type: HUMAN OTC DRUG LABEL
Date: 20130404

ACTIVE INGREDIENTS: TITANIUM DIOXIDE 11.52 g/60 mL; Zinc Oxide 2.772 g/60 mL
INACTIVE INGREDIENTS: CYCLOMETHICONE 5; DIMETHICONE 100; C12-15 ALKYL BENZOATE; CAPRYLIC/CAPRIC ACID; DIMETHICONE/VINYL DIMETHICONE CROSSPOLYMER (HARD PARTICLE); TOCOTRIENOLS; TOCOPHEROL; RICE BRAN; SQUALANE; LAVENDER OIL; SOYBEAN; DIMETHICONE; LINOLEIC ACID; OMEGA-3 FATTY ACIDS; CAPRYLYL GLYCOL; ALUMINUM OXIDE; PHENOXYETHANOL; TRIETHOXYCAPRYLYLSILANE; FERRIC OXIDE RED

Active Ingredients

Titanium Dioxide 4.8%

Zinc Oxide 3.0%

Purpose

Sunscreen

Keep Out of Reach of Children.

If swallowed, get medical help or contact a Poison Control Center right away.

Uses

- helps prevent sunburn
- if used as directed with other sun protection measures (see Directions), decreases the risk of skin cancer and early skin againg caused by the sun

Warnings

Do

For external use only.

Do not use on damaged or broken skin.

When using this product keep out of reach of eyes. Rinse with water to remove.

Stop use and ask a doctor if rsh occurs.

Directions

- apply liberally 15 minutes before sun exposure
- reapply at least ever 2 hours
- use a water resistant sunscreen if swimming or sweating
- Sun Protection Measures: Spending time in the sun increases your risk of skin cancer and early skin aging. To decrease this risk, regularly use a sunscreen with a broad spectrum SPF of 15 or higher and other sun protection measures, including:
- limit time in the sun, especially from 10 a.m.-2 p.m.
- wear long-sleeve shirts, pants, hats and sunglasses
- children under 6 months of age: ask a doctor

Inactive Ingredients

cyclopentasiloxane, dimethicone crosspolymer, c12-15 alkyl benzoate, caprylic/capric triglyceride, dimethicone/vinyl dimethicone crosspolymer,